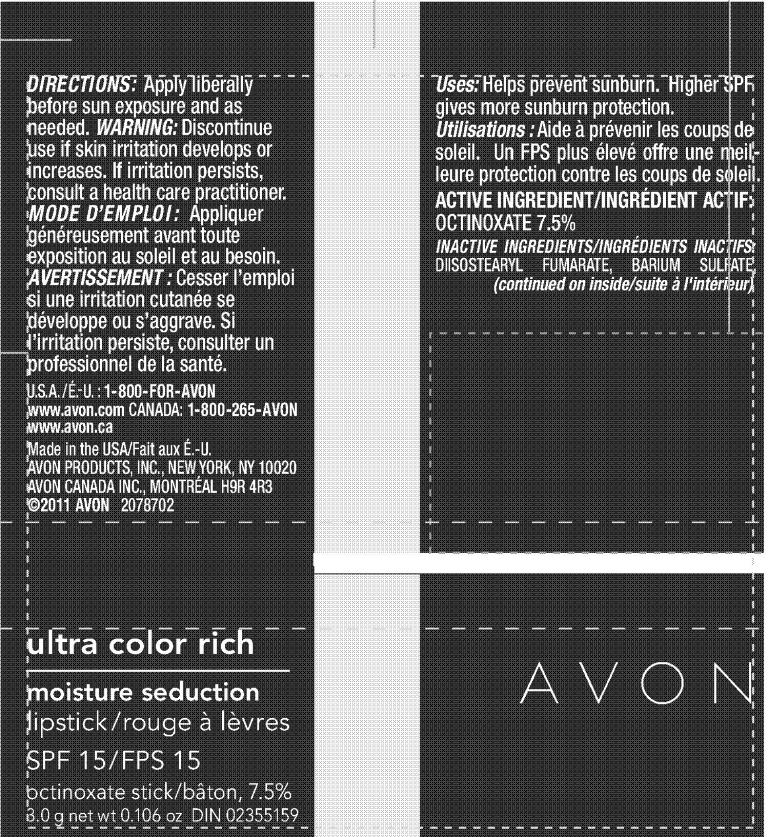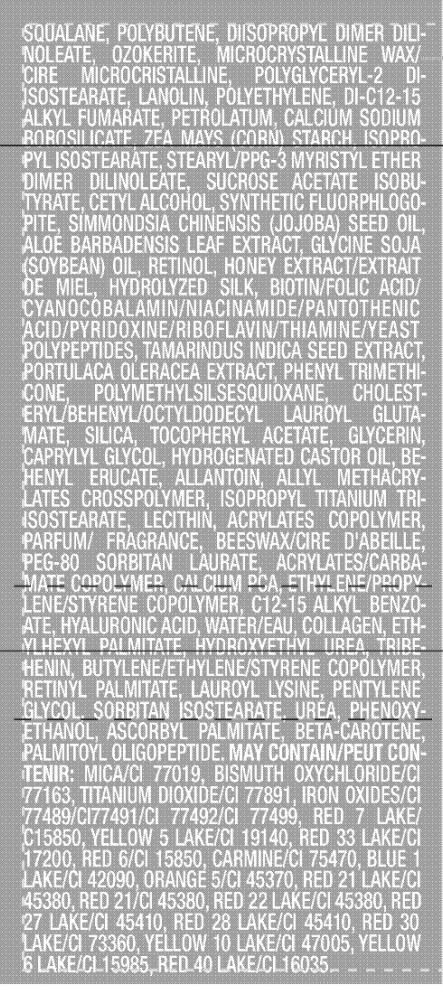 DRUG LABEL: Ultra Color Rich
NDC: 10096-0229 | Form: LIPSTICK
Manufacturer: Avon Products, Inc.
Category: otc | Type: HUMAN OTC DRUG LABEL
Date: 20101214

ACTIVE INGREDIENTS: OCTINOXATE 0.225 g/3 g
INACTIVE INGREDIENTS: SQUALANE; MICROCRYSTALLINE WAX; LANOLIN; PETROLATUM; SUCROSE ACETATE ISOBUTYRATE; CETYL ALCOHOL; RETINOL; PHENYL TRIMETHICONE; GLYCERIN; CAPRYLYL GLYCOL; HYDROGENATED CASTOR OIL; ALLANTOIN; C12-15 ALKYL BENZOATE; HYALURONIC ACID; WATER; ETHYLHEXYL PALMITATE; HYDROXYETHYL UREA; TRIBEHENIN; LAUROYL LYSINE; PENTYLENE GLYCOL; UREA; PHENOXYETHANOL; ASCORBYL PALMITATE; BETA CAROTENE; PALMITOYL OLIGOPEPTIDE; MICA; BISMUTH OXYCHLORIDE; TITANIUM DIOXIDE; BARIUM SULFATE

DOSAGE AND ADMINISTRATION

DIRECTIONS: Apply liberally
before sun exposure and as needed.

WARNINGS

WARNING: Discontinue
use if skin irritation develops or
increases. If irritation persists,
consult a health care practitioner.

INDICATIONS AND USAGE

Uses: Helps prevent sunburn. Higher SPF
gives more sunburn protection.

ACTIVE INGREDIENT/INGRÉDIENT ACTIF:
OCTINOXATE 7.5%

INACTIVE INGREDIENTS/INGRÉDIENTS INACTIFS:
DIISOSTEARYL FUMARATE, BARIUM SULFATE,SQUALANE, POLYBUTENE, DIISOPROPYL DIMER DILINOLEATE,
OZOKERITE, MICROCRYSTALLINE WAX/
CIRE MICROCRISTALLINE, POLYGLYCERYL-2 DIISOSTEARATE,
LANOLIN, POLYETHYLENE, DI-C12-15
ALKYL FUMARATE, PETROLATUM, CALCIUM SODIUM
BOROSILICATE, ZEA MAYS (CORN) STARCH, ISOPROPYL
ISOSTEARATE, STEARYL/PPG-3 MYRISTYL ETHER
DIMER DILINOLEATE, SUCROSE ACETATE ISOBUTYRATE,
CETYL ALCOHOL, SYNTHETIC FLUORPHLOGOPITE,
SIMMONDSIA CHINENSIS (JOJOBA) SEED OIL,
ALOE BARBADENSIS LEAF EXTRACT, GLYCINE SOJA
(SOYBEAN) OIL, RETINOL, HONEY EXTRACT/EXTRAIT
DE MIEL, HYDROLYZED SILK, BIOTIN/FOLIC ACID/
CYANOCOBALAMIN/NIACINAMIDE/PANTOTHENIC
ACID/PYRIDOXINE/RIBOFLAVIN/THIAMINE/YEAST
POLYPEPTIDES, TAMARINDUS INDICA SEED EXTRACT,
PORTULACA OLERACEA EXTRACT, PHENYL TRIMETHICONE,
POLYMETHYLSILSESQUIOXANE, CHOLESTERYL/
BEHENYL/OCTYLDODECYL LAUROYL GLUTAMATE,
SILICA, TOCOPHERYL ACETATE, GLYCERIN,
CAPRYLYL GLYCOL, HYDROGENATED CASTOR OIL, BEHENYL
ERUCATE, ALLANTOIN, ALLYL METHACRYLATES
CROSSPOLYMER, ISOPROPYL TITANIUM TRIISOSTEARATE,
LECITHIN, ACRYLATES COPOLYMER,
PARFUM/ FRAGRANCE, BEESWAX/CIRE D'ABEILLE,
PEG-80 SORBITAN LAURATE, ACRYLATES/CARBAMATE
COPOLYMER, CALCIUM PCA, ETHYLENE/PROPYLENE/
STYRENE COPOLYMER, C12-15 ALKYL BENZOATE,
HYALURONIC ACID, WATER/EAU, COLLAGEN, ETHYLHEXYL
PALMITATE, HYDROXYETHYL UREA, TRIBEHENIN,
BUTYLENE/ETHYLENE/STYRENE COPOLYMER,
RETINYL PALMITATE, LAUROYL LYSINE, PENTYLENE
GLYCOL, SORBITAN ISOSTEARATE, UREA, PHENOXYETHANOL,
ASCORBYL PALMITATE, BETA-CAROTENE,
PALMITOYL OLIGOPEPTIDE. MAY CONTAIN/PEUT CONTENIR:
MICA/CI 77019, BISMUTH OXYCHLORIDE/CI
77163, TITANIUM DIOXIDE/CI 77891, IRON OXIDES/CI
77489/CI77491/CI 77492/CI 77499, RED 7 LAKE/
C15850, YELLOW 5 LAKE/CI 19140, RED 33 LAKE/CI
17200, RED 6/CI 15850, CARMINE/CI 75470, BLUE 1
LAKE/CI 42090, ORANGE 5/CI 45370, RED 21 LAKE/CI
45380, RED 21/CI 45380, RED 22 LAKE/CI 45380, RED
27 LAKE/CI 45410, RED 28 LAKE/CI 45410, RED 30
LAKE/CI 73360, YELLOW 10 LAKE/CI 47005, YELLOW
6 LAKE/CI 15985, RED 40 LAKE/CI 16035.